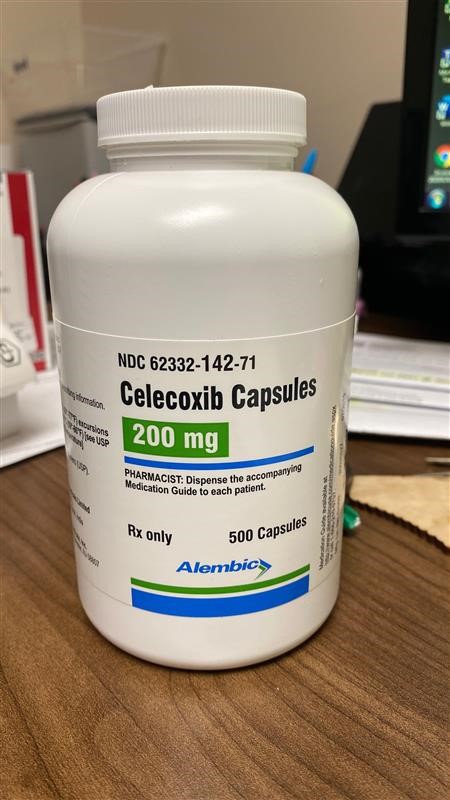 DRUG LABEL: celecoxib
NDC: 80175-0142 | Form: CAPSULE
Manufacturer: Central Packaging
Category: prescription | Type: HUMAN PRESCRIPTION DRUG LABEL
Date: 20210222

ACTIVE INGREDIENTS: CELECOXIB 200 mg/1 1

CONTRAINDICATIONS

Celecoxib is contraindicated in the following patients: · Known hypersensitivity (e.g., anaphylactic reactions and serious skin reactions)to celecoxib, any components of the drug product [see Warnings and Precautions (5.7, 5.9)].· History of asthma, urticaria, or other allergic-type reactions after taking aspirin or other NSAIDs. Severe, sometimes fatal, anaphylactic reactions to NSAIDs, have been reported in such patients [see Warnings and Precautions (5.7, 5.8)]. · In the setting of coronary artery bypass graft (CABG) surgery [see Warnings and Precautions (5.1)].· In patients who have demonstrated allergic-type reactions to sulfonamides.

LABORATORY TESTS

Because serious GI bleeding, hepatotoxicity, and renal injury can occur without warning symptoms or signs, consider monitoring patients on long-term NSAID treatment with a CBC and a chemistry profile periodically [see Warnings and Precautions (5.2, 5.3, 5.6)]. In controlled clinical trials, elevated BUN occurred more frequently in patients receiving celecoxib compared with patients on placebo. This laboratory abnormality was also seen in patients who received comparator NSAIDs in these studies. The clinical significance of this abnormality has not been established.

DOSAGE FORMS AND STRENGTHS

Celecoxib capsules: 50 mg are opaque white/opaque white hard gelatin capsules size “5” having imprinting “134” on body with red ink and “A” on cap with red ink filled with white to off-white colored granular powder. 100 mg are opaque white/opaque white hard gelatin capsules size “3” having imprinting “135” on body with blue ink and “A” on cap with blue ink filled with white to off-white colored granular powder. 200 mg are opaque white/opaque white hard gelatin capsules size “1” having imprinting “136” on body with golden yellow ink and “A” on cap with golden yellow ink filled with white to off-white colored granular powder. 400 mg are opaque white/opaque white hard gelatin capsules size “00” having imprinting “137” on body with green ink and “A” on cap with green ink filled with white to off-white colored granular powder.

Medication Guide
for
Non-Steroidal Anti-Inflammatory Drugs (NSAIDs)
(See the end of this Medication Guide for a list of prescription NSAID medicines.)

What is the most important information I should know about medicines called Non-Steroidal Anti-Inflammatory Drugs (NSAIDs)?

NSAID medicines may increase the chance of a heart attack or stroke that can lead to death.

This chance increases:

with longer use of NSAID medicines
in people who have heart disease

NSAID medicines should never be used right before or after a heart surgery called a "coronary artery bypass graft (CABG)."

NSAID medicines can cause ulcers and bleeding in the stomach and intestines at any time during treatment. Ulcers and bleeding:

can happen without warning symptoms
may cause death

The chance of a person getting an ulcer or bleeding increases with:

taking medicines called "corticosteroids" and "anticoagulants"
longer use
smoking
drinking alcohol
older age
having poor health

NSAID medicines should only be used:

exactly as prescribed
at the lowest dose possible for your treatment
for the shortest time needed

What are Non-Steroidal Anti-Inflammatory Drugs (NSAIDs)?

NSAID medicines are used to treat pain and redness, swelling, and heat (inflammation) from medical conditions such as:

different types of arthritis
menstrual cramps and other types of short-term pain

Who should not take a Non-Steroidal Anti-Inflammatory Drug (NSAID)?

Do not take an NSAID medicine:

if you had an asthma attack, hives, or other allergic reaction with aspirin or any other NSAID medicine
for pain right before or after heart bypass surgery

Tell your healthcare provider:

about all of your medical conditions.
about all of the medicines you take. NSAIDs and some other medicines can interact with each other and cause serious side effects. Keep a list of your medicines to show to your healthcare provider and pharmacist.
if you are pregnant. NSAID medicines should not be used by pregnant women late in their pregnancy.
if you are breastfeeding. Talk to your doctor.

What are the possible side effects of Non-Steroidal Anti-Inflammatory Drugs (NSAIDs)?

Serious side effects include: Other side effects include:

heart attack
stroke
high blood pressure
heart failure from body swelling (fluid retention)
kidney problems including kidney failure
bleeding and ulcers in the stomach and intestine
low red blood cells (anemia)
life-threatening skin reactions
life-threatening allergic reactions
liver problems including liver failure
asthma attacks in people who have asthma

stomach pain
constipation
diarrhea
gas
heartburn
nausea
vomiting
dizziness

Get emergency help right away if you have any of the following symptoms:

shortness of breath or trouble breathing
chest pain
weakness in one part or side of your body

slurred speech
swelling of the face or throat

Stop your NSAID medicine and call your healthcare provider right away if you have any of the following symptoms:

nausea
more tired or weaker than usual
itching
your skin or eyes look yellow
stomach pain
flu-like symptoms

vomit blood
there is blood in your bowel movement or it is black and sticky like tar
skin rash or blisters with fever
unusual weight gain
swelling of the arms and legs, hands and feet

These are not all the side effects with NSAID medicines. Talk to your healthcare provider or pharmacist for more information about NSAID medicines.

Call your doctor for medical advice about side effects. You may report side effects to FDA at 1-800-FDA-1088.

Other information about Non-Steroidal Anti-Inflammatory Drugs (NSAIDs)

Aspirin is an NSAID medicine but it does not increase the chance of a heart attack. Aspirin can cause bleeding in the brain, stomach, and intestines. Aspirin can also cause ulcers in the stomach and intestines.
Some of these NSAID medicines are sold in lower doses without a prescription (over –the –counter). Talk to your healthcare provider before using over –the –counter NSAIDs for more than 10 days.

NSAID medicines that need a prescription
Generic Name Tradename
*Vicoprofen contains the same dose of ibuprofen as over-the-counter (OTC) NSAIDs, and is usually used for less than 10 days to treat pain. The OTC NSAID label warns that long term continuous use may increase the risk of heart attack or stroke.